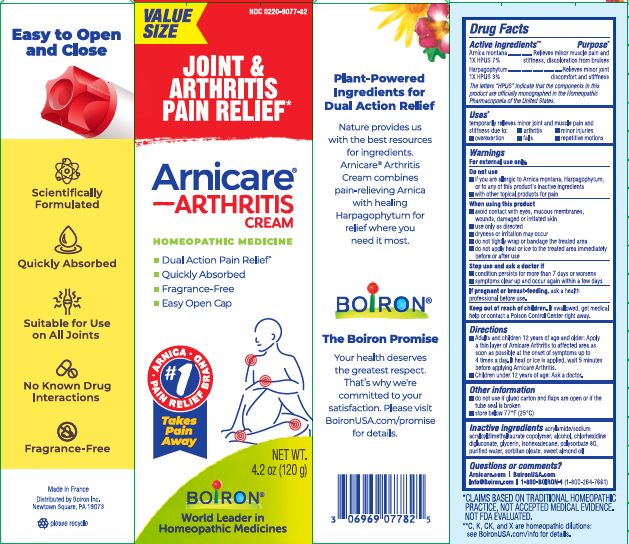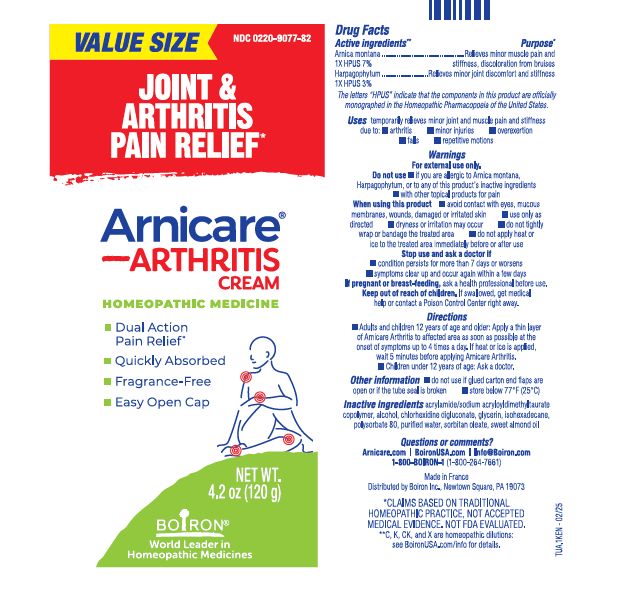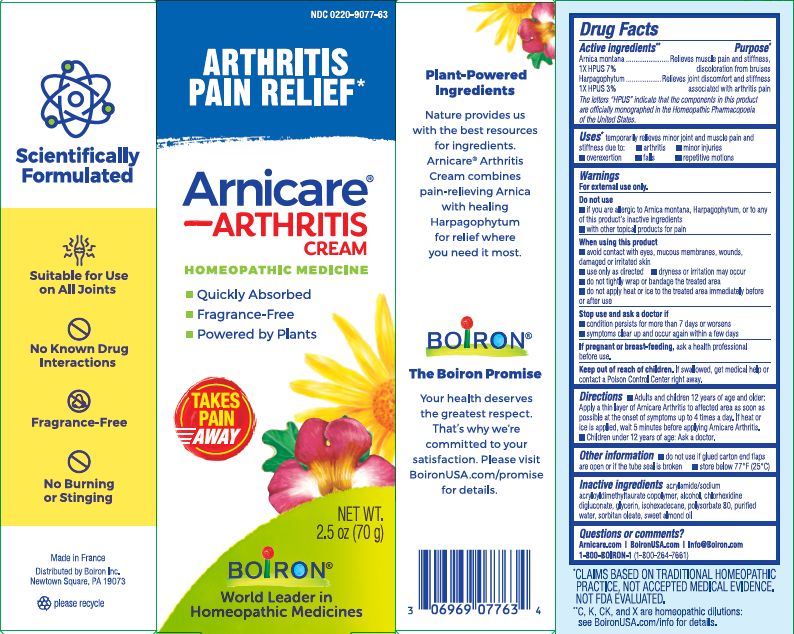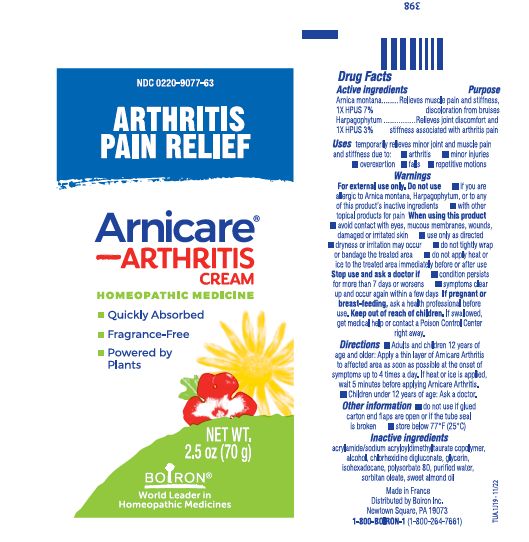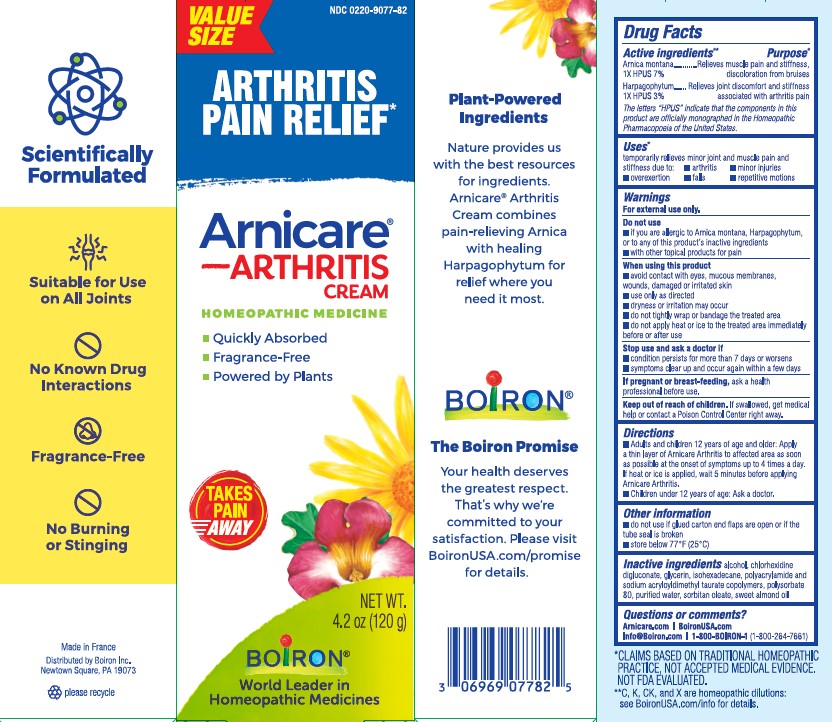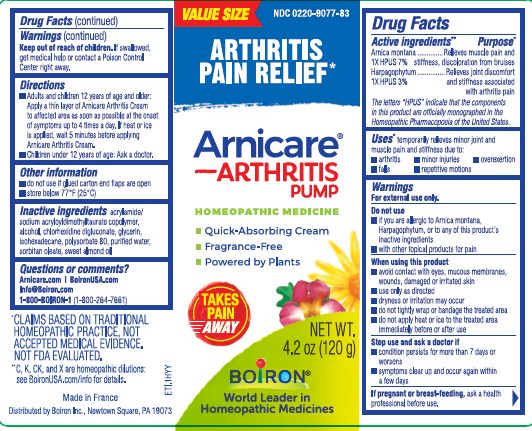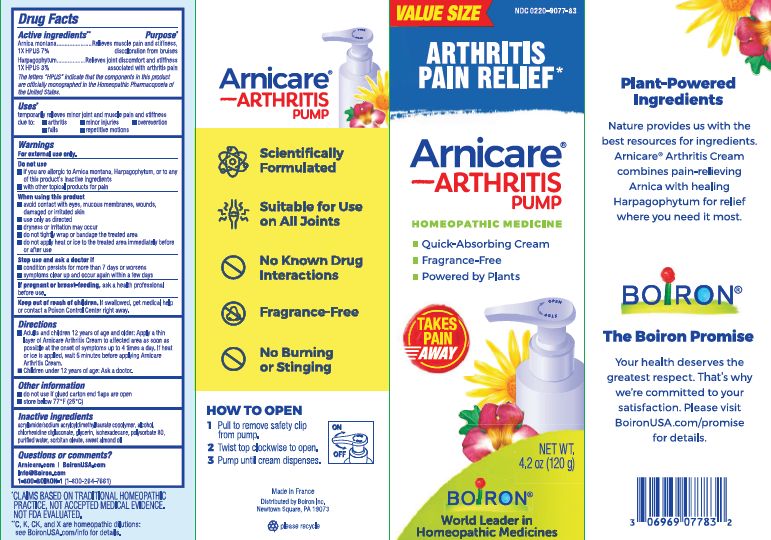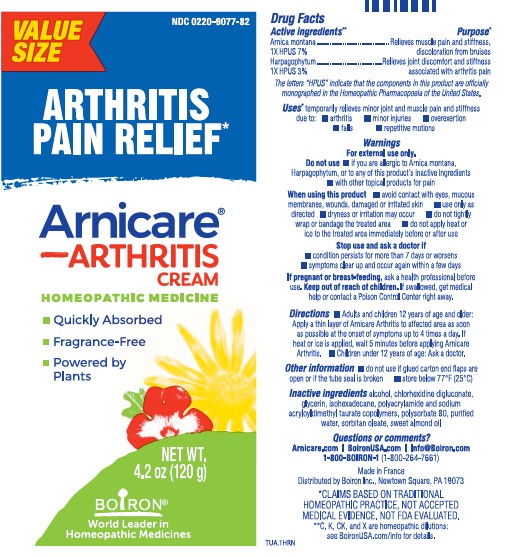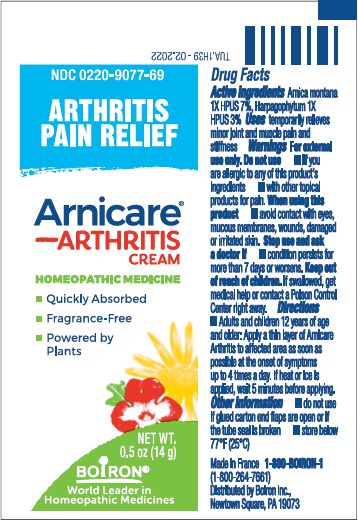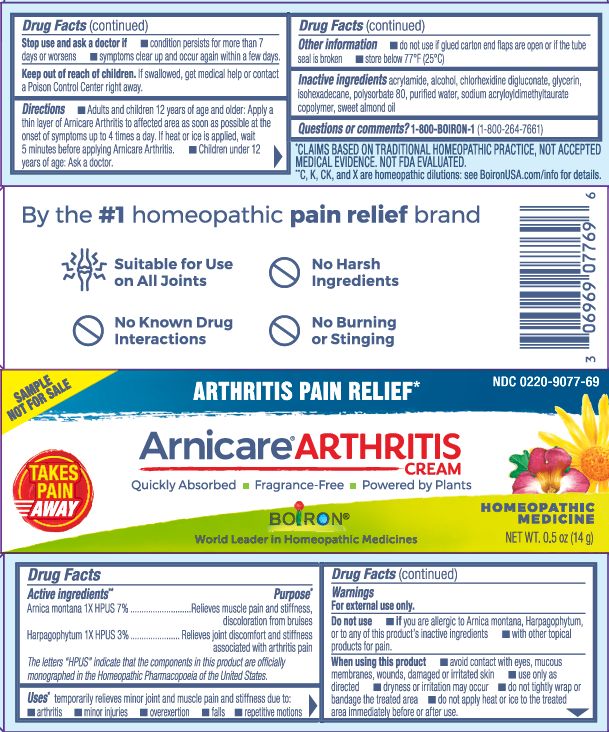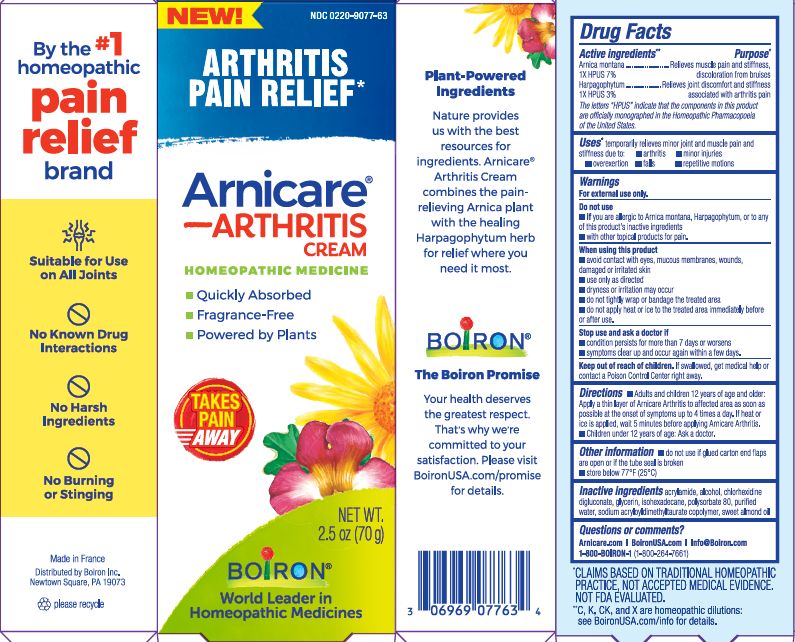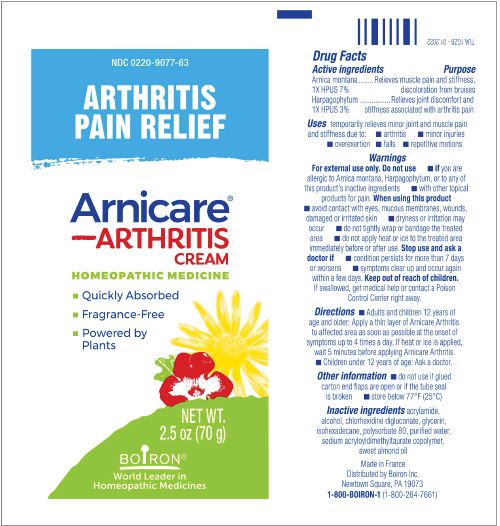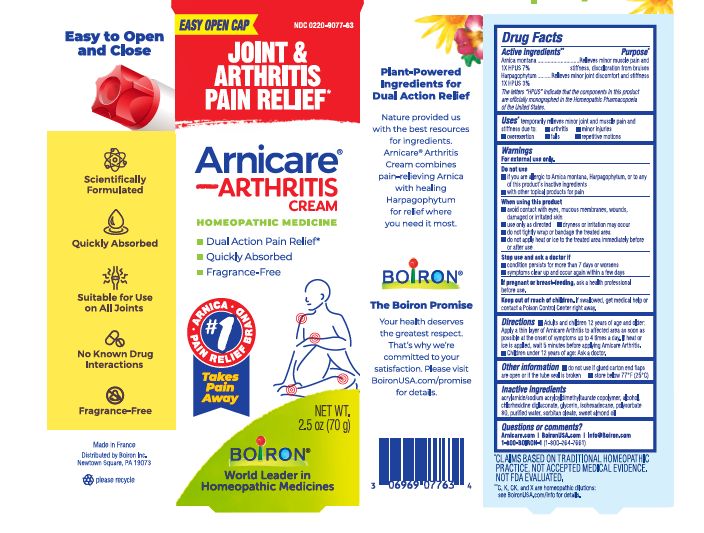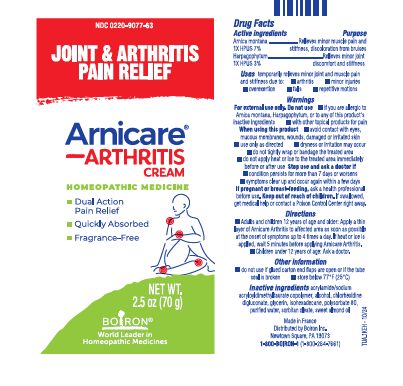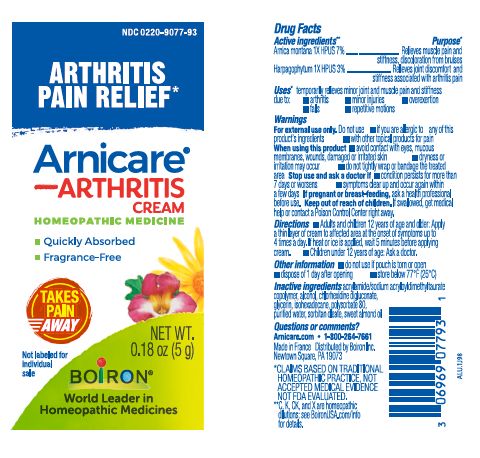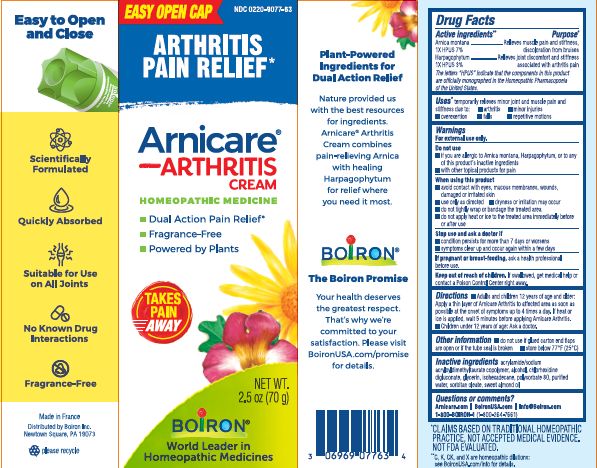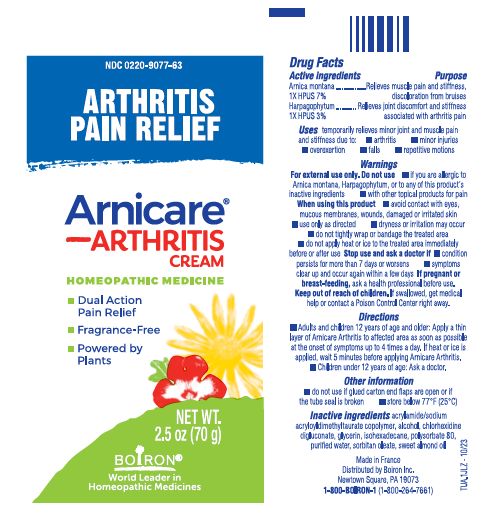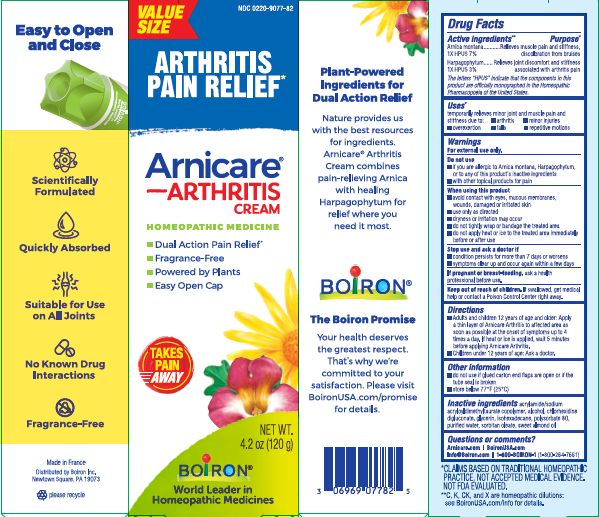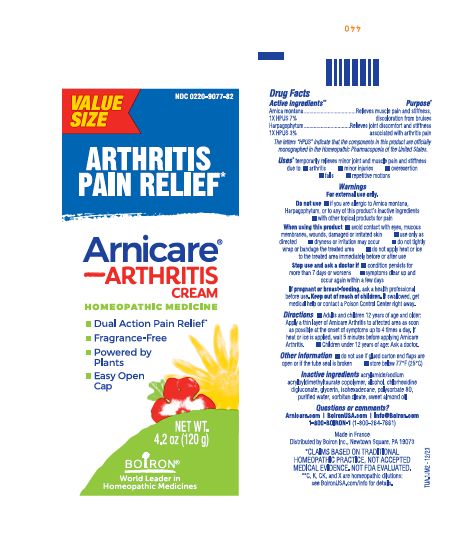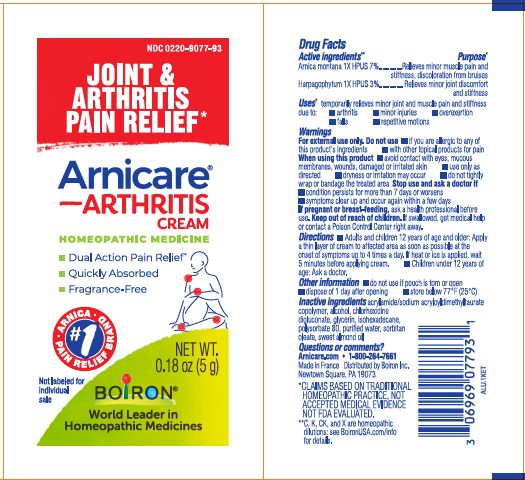 DRUG LABEL: ARNICARE ARTHRITIS
NDC: 0220-9077 | Form: CREAM
Manufacturer: Boiron
Category: homeopathic | Type: HUMAN OTC DRUG LABEL
Date: 20250512

ACTIVE INGREDIENTS: HARPAGOPHYTUM PROCUMBENS ROOT 1 [hp_X]/1 g; HARPAGOPHYTUM ZEYHERI ROOT 1 [hp_X]/1 g; ARNICA MONTANA 1 [hp_X]/1 g
INACTIVE INGREDIENTS: ALCOHOL; WATER; SODIUM ACRYLOYLDIMETHYLTAURATE-ACRYLAMIDE COPOLYMER (1:1; 90000-150000 MPA.S); POLYSORBATE 80; ACRYLAMIDE; CHLORHEXIDINE GLUCONATE; SORBITAN MONOOLEATE; GLYCERIN; ISOHEXADECANE; ALMOND OIL

Arnicare Arthritis Cream

Active ingredients**

Arnica montana 1X HPUS 7%

Harpagophytum 1X HPUS 3%

The letters "HPUS" indicate that the components in this product are officially monographed in the Homeopathic Pharmacopoeia of the United States.

Purpose*

Arnica montana 1X HPUS 7% ... Relieves minor muscle pain and stiffness, discoloration from bruises

Harpagophytum 1X HPUS 3% ... Relieves minor joint discomfort and stiffness

Uses*

temporarily relieves minor joint and muscle pain and stiffness due to:

arthritis
minor injuries
overexertion
falls
repetitive motions

WARNINGS

For external use only.

DO NOT USE

- if you are allergic to Arnica montana, Harpagophytum or to any of this product's inactive ingredients
- with other topical products for pain

WHEN USING

- avoid contact with eyes, mucous membranes, wounds, damaged or irritated skin
- use only as directed
- dryness or irritation may occur
- do not tightly wrap or bandage the treated area
- do not apply heat or ice to the treated area immediately before or after use

Stop use and ask a doctor if

- conditions persists for more than 7 days or worsens
- symptoms clear up and occur again within a few days

PREGNANCY OR BREAST FEEDING

If pregnant or breast-feeding, ask a health professional before use.

Keep out of reach of children. If swallowed, get medical help or contact a Poison Control Center right away.

Directions

- Adults and children 12 years of age and older: Apply a thin layer of Arnicare Arthritis to affected area as soon as possible at the onset of symptoms up to 4 times a day. If heat or ice is applied, wait 5 minutes before applying Arnicare Arthritis.
- Children under 12 years of age: Ask a doctor.

- do not use if glued carton end flaps are open or if the tube seal is broken
- store below 77° F (25° C)
- do not use if pouch is torn or open
- dispose of 1 day after opening

INACTIVE INGREDIENT

acrylamide/sodium acryloyldimethyltaurate copolymer , alcohol, chlorhexidine digluconate, glycerin, isohexadecane, polysorbate 80, purified water, sorbitan oleate, sweet almond oil

Questions or comments?

Arnicare.com

BoironUSA.com

Info@Boiron.com

1-800-BOIRON-1 (1-800-264-7661)

Made in France

Distributed by Boiron, Inc.

Newtown Square, PA 19073

0.18 oz (5 g)

0.5 oz (14 g)

2.5 oz (70 g)

4.2 oz (120 g)

Joint & Arthritis Pain Relief*

Quickly-Absorbed

Fragrance-Free

No Known Drug Interactions

Dual Action Pain Relief*

4.2 oz (120g) Pump:

HOW TO OPEN

1 Pull to remove safety clip from pump.

2 Twist top clockwise to open.

3 Pump until cream dispense.

*CLAIMS BASED ON TRADITIONAL HOMEOPATHIC PRACTICE NOT ACCEPTED MEDICAL EVIDENCE. NOT FDA EVALUATED.
**C,K,CK, and X are homeopathic dilutions: see BoironUSA.com/info for details.